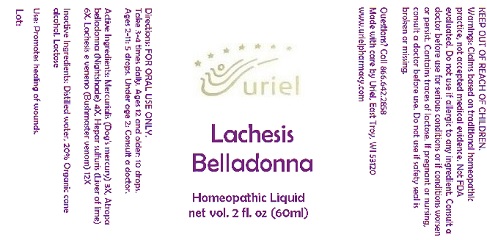 DRUG LABEL: Lachesis Belladonna
NDC: 48951-6013 | Form: LIQUID
Manufacturer: Uriel Pharmacy Inc.
Category: homeopathic | Type: HUMAN OTC DRUG LABEL
Date: 20180427

ACTIVE INGREDIENTS: MERCURIALIS PERENNIS 3 [hp_X]/1 mL; ATROPA BELLADONNA 4 [hp_X]/1 mL; CALCIUM SULFIDE 6 [hp_X]/1 mL; LACHESIS MUTA VENOM 12 [hp_X]/1 mL
INACTIVE INGREDIENTS: WATER; ALCOHOL; LACTOSE

Lachesis Belladonna

INDICATIONS AND USAGE

Directions: FOR ORAL USE ONLY.

DOSAGE AND ADMINISTRATION

Take 3-4 times daily. Ages 12 and older: 10 drops. Ages 2-11: 5 drops. Under age 2: Consult a doctor.

ACTIVE INGREDIENT

Active Ingredients: Mercurialis (Dog's mercury) 3X, Atropa belladonna (Nightshade) 4X, Hepar sulfuris (Liver of lime) 6X, Lachesis e veneno (Bushmaster venom) 12X

INACTIVE INGREDIENT

Inactive Ingredients: Distilled water, 20% Organic cane alcohol, Lactose

PURPOSE

Use: Promotes healing of wounds.

KEEP OUT OF REACH OF CHILDREN.

WARNINGS

Warnings: Claims based on traditional homeopathic practice, not accepted medical evidence. Not FDA evaluated. Do not use if allergic to any ingredient. Consult a doctor before use for serious conditions or if conditions worsen or persist. Contains traces of lactose. If pregnant or nursing, consult a doctor before use. Do not use if safety seal is broken or missing.

QUESTIONS

Questions? Call 866.642.2858 Made with care by Uriel, East Troy, WI 53120 www.urielpharmacy.com